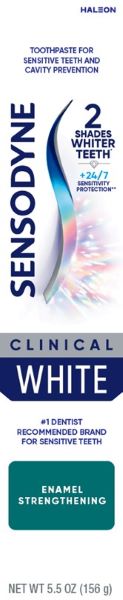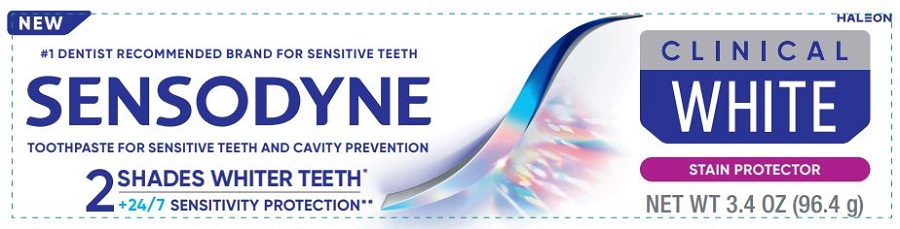 DRUG LABEL: Sensodyne

NDC: 0135-0702 | Form: PASTE
Manufacturer: Haleon US Holdings LLC
Category: otc | Type: HUMAN OTC DRUG LABEL
Date: 20250625

ACTIVE INGREDIENTS: POTASSIUM NITRATE 50 mg/1 g; SODIUM FLUORIDE 2.5 mg/1 g
INACTIVE INGREDIENTS: SORBITOL; HYDRATED SILICA; GLYCERIN; SODIUM TRIPOLYPHOSPHATE ANHYDROUS; POLYETHYLENE GLYCOL 400; SODIUM LAURYL SULFATE; ALUMINUM OXIDE; TITANIUM DIOXIDE; XANTHAN GUM; COCAMIDOPROPYL BETAINE; SODA LIME; CARRAGEENAN; SACCHARIN SODIUM

Drug Facts

Active ingredients

Potassium nitrate 5%
Sodium fluoride 0.25% (0.15% w/v fluoride ion)

Purposes

Antihypersensitivity
Anticavity

Uses

- builds increasing protection against painful sensitivity of the teeth to cold, heat, acids, sweets, or contact.
- aids in the prevention of dental cavities.

Warnings

Stop use and ask a dentist if

- the problem persists or worsens. Sensitive teeth may indicate a serious problem that may need prompt care by a dentist.
- pain/sensitivity still persists after 4 weeks of use.

Keep out of reach of children.

If more than used for brushing is accidentally swallowed, get medical help or contact a Poison Control Center right away.

Directions

- adults and children 12 years of age and older:
- apply at least a 1-inch strip of the product onto a soft bristle toothbrush.
- brush teeth thoroughly for at least 1 minute twice a day (morning and evening), and not more than 3 times a day, or as recommended by a dentist or doctor. Make sure to brush all sensitive areas of the teeth. Minimize swallowing. Spit out after brushing.
- children under 12 years of age:Consult a dentist or doctor.

Other information

- do not store above 25°C (77°F)

Inactive ingredients

water, sorbitol, hydrated silica, glycerin, pentasodium triphosphate, PEG-8, sodium lauryl sulfate, flavor, alumina, titanium dioxide, xanthan gum, cocamidopropyl betaine, sodium hydroxide, carrageenan, sodium saccharin

Questions or comments?

1-866-844-2797

Additional Information (Enamel Strengthening)

ALWAYS FOLLOW THE LABEL

SENSODYNE CLINICAL WHITE

CLINICALLY PROVEN WHITENINGDESIGNED FOR SENSITIVE TEETH

WHITENING

Clinically proven whitening ingredients remove stains, polish teeth and help prevent future stains

SENSITIVITY PROTECTION

Clinically proven ingredients to protect against sensitivity and strengthen enamel.

Strengthens enamel

ENAMEL SAFE

* As shown in an 8 week study.
** With twice daily brushing.

Additional Information (Stain Protector)

ALWAYS FOLLOW THE LABEL

SENSODYNE

CLINICAL
WHITE

CLINICAL PROVEN
WHITENING
DESIGNED FOR
SENSITIVE TEETH

WHITENING
Clinically proven whitening ingredients remove stains, polish teeth and help prevent future stains

SENSITIVITY PROTECTION

Clinically proven ingredients to protect against sensitivity and strengthen enamel

Helps protect teeth from future stains

ENAMEL SAFE

* As shown in an 8 week study.
** With twice daily brushing.

Distributed by: Haleon, Warren, NJ 07059
Trademarks owned or licensed by Haleon.
© 2023 Haleon or licensor.

Principal Display Panel (Enamel Strengthening)

HALEON

TOOTHPASE FOR SENSITIVE TEETH AND CAVITY PREVENTION

SENSODYNE

2 SHADES WHITER TEETH*

+24/7 SENSITIVITY PROTECTION**

CLINICAL

WHITE

#1 DENTIST RECOMMENDED BRAND FOR SENSITIVE TEETH

ENAMEL STRENGTHENING

NET WT 5.5 OZ (156 g)

Principal Display Panel (Stain Protector)

NEW

#1 DENTIST RECOMMENDED BRAND FOR SENSITIVE TEETH

SENSODYNE

TOOTHPASTE FOR SENSITIVE TEETH AND CAVITY PREVENTION

2 SHADES WHITER TEETH*
+24/7 SENSITIVITY PROTECTION**

CLINICAL
WHITE

STAIN PROTECTOR

NET WT 3.4 OZ (96.4 g)